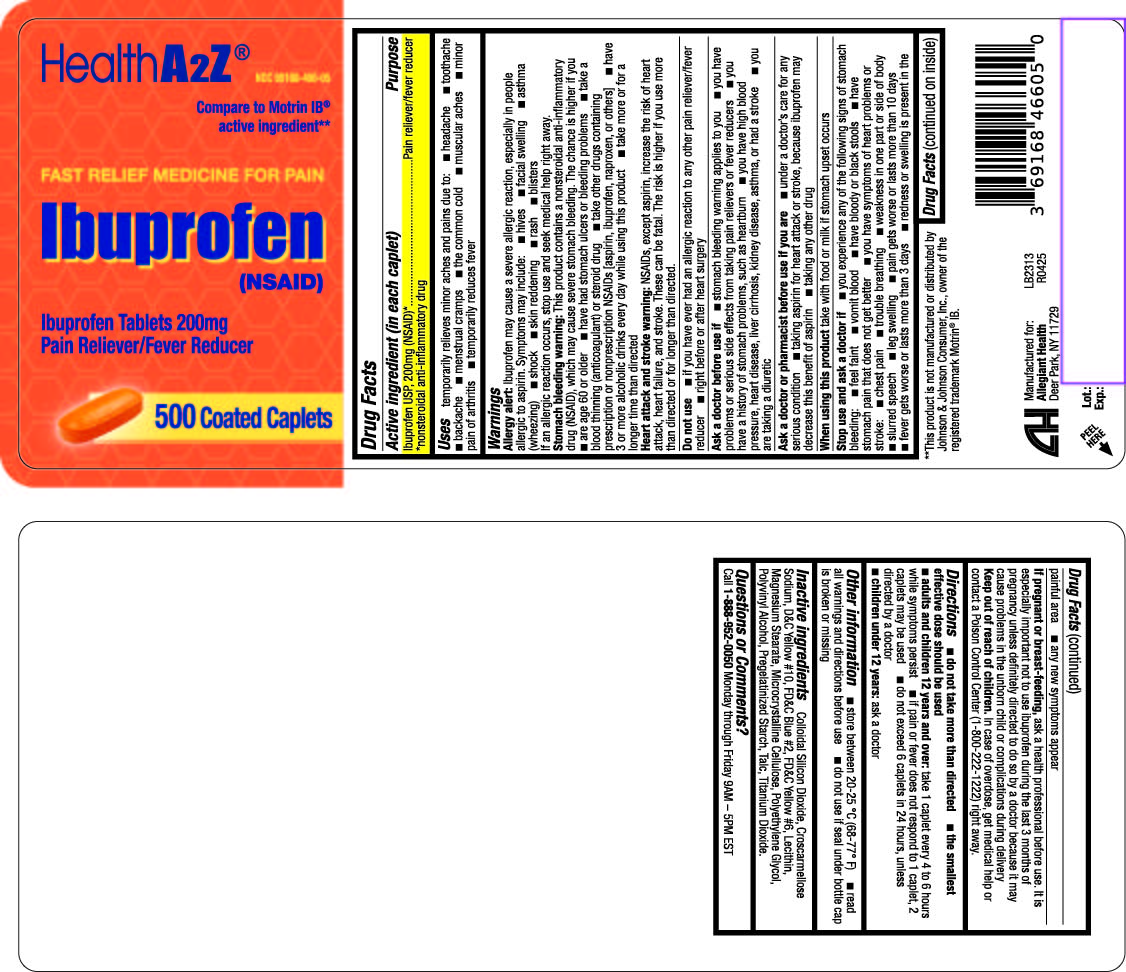 DRUG LABEL: Ibuprofen
NDC: 69168-466 | Form: TABLET, FILM COATED
Manufacturer: Allegiant Health
Category: otc | Type: HUMAN OTC DRUG LABEL
Date: 20250414

ACTIVE INGREDIENTS: IBUPROFEN 200 mg/1 1
INACTIVE INGREDIENTS: SILICON DIOXIDE; CROSCARMELLOSE SODIUM; D&C YELLOW NO. 10; FD&C BLUE NO. 2; FD&C YELLOW NO. 6; LECITHIN, SOYBEAN; MAGNESIUM STEARATE; MICROCRYSTALLINE CELLULOSE; POLYETHYLENE GLYCOL, UNSPECIFIED; POLYVINYL ALCOHOL; STARCH, CORN; TALC; TITANIUM DIOXIDE

466 - Ibuprofen 200mg Caplet

Active ingredient(s)

Ibuprofen USP, 200mg (NSAID)*

*nonsteroidal anti-inflammatory drug

Purpose

Pain reliever/fever reducer

Use(s)

temporarily relieves minor aches and pains due to:

- headache
- toothache
- backache
- menstrual cramps
- the common cold
- muscular aches n minor pain of arthritis
- temporarily reduces fever

Warnings

Allergy alert: Ibuprofen may cause a severe allergic reaction, especially in people allergic to aspirin. Symptoms may include: hives facial swelling asthma (wheezing) shock skin reddening rash blisters If an allergic reaction occurs, stop use and seek medical help right away.

Stomach bleeding warning: This product contains an NSAID, which may cause severe stomach bleeding. The chance is higher if you: are age 60 or older have had stomach ulcers or bleeding problems take a blood thinning (anticoagulant) or steroid drug take other drugs containing prescription or nonprescription NSAIDs (aspirin, ibuprofen, naproxen, or others) have 3 or more alcoholic drinks every day while using this product take more or for a longer time than directed

Heart attack and stroke warning: NSAIDs, except aspirin, increase the risk of heart attack, heart failure, and stroke. These can be fatal. The risk is higher if you use more than directed or for longer than directed.

Do not use if you have

ever had an allergic reaction to ibuprofen or any other pain reliever/fever reducer right before or after heart surgery

Ask a doctor before use if you

- have problems or serious side effects from taking pain relievers or fever reducers

- the stomach bleeding warning applies to you
- you have a history of stomach problems, such as heartburn
- you have high blood pressure, heart disease, liver cirrhosis, kidney disease, asthma, or had a stroke
- you are taking a diuretic

Ask a doctor or pharmacist before use if

you are

- taking aspirin for heart attack or stroke, because ibuprofen may decrease this benefit of aspirin
- under a doctor's care for any serious condition
- taking any other drug

When using this product

take with food or milk if stomach upset occurs

Stop use and ask a doctor if

- you experience any of the following signs of stomach bleeding:
- feel faint
- vomit blood
- have bloody or black stools
- have stomach pain that does not get better
- you have symptoms of heart problems or stroke:
  - chest pain
  - trouble breathing
  - weakness in one part or side of body
  - slurred speech
  - leg swelling
- pain gets worse or lasts more than 10 days
- fever gets worse or lasts more than 3 days
- redness or swelling is present in the painful area
- any new symptoms appear

If pregnant or breastfeeding,

ask a health professional before use. It is especially important not to use ibuprofen during the last 3 months of pregnancy unless definitely directed to do so by a doctor because it may cause problems in the unborn child or complications during delivery.

Keep out of reach of children

In case of overdose, get medical help or contact a Poison Control Center right away. (1-800-222-1222)

Directions

- do not take more than directed
- the smallest effective dose should be used
- adults and children 12 years and older
- take 1 caplet every 4 to 6 hours while symptoms persist
- if pain or fever does not respond to 1 caplet, 2 caplets may be used
- do not exceed 6 caplets in 24 hours, unless directed by a doctor
- children under 12 years
- ask a doctor

Other information

- store between 20-25 °C (68-77° F)
- read all warnings and directions before use
- do not use if seal under bottle cap is broken or missing

Inactive ingredients

Colloidal Silicon Dioxide, Croscarmellose Sodium, D&C Yellow #10, FD&C Blue #2, FD&C Yellow #6,
Lecithin, Magnesium Stearate, Microcrystalline Cellulose, Polyethylene Glycol, Polyvinyl Alcohol, Pregelatinized
Starch, Talc, Titanium Dioxide.

Questions/Comments

Call 1-888-952-0050

(Monday-Friday 9 AM – 5 PM EST)

Principal Display Panel

Ibuprofen 200mg